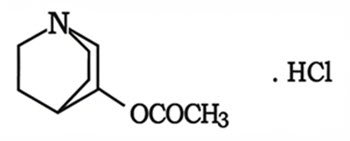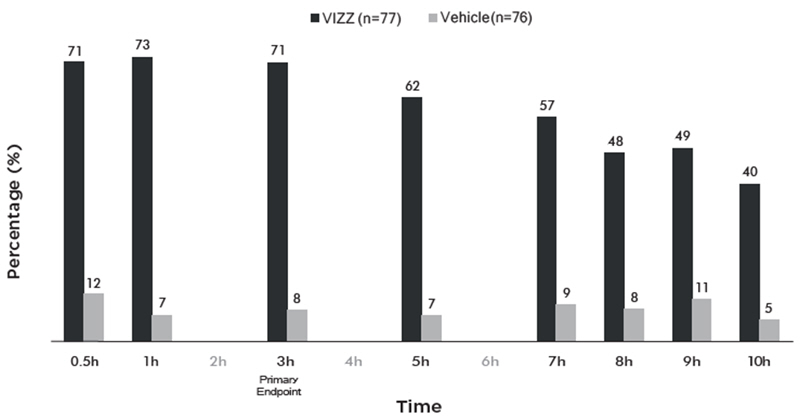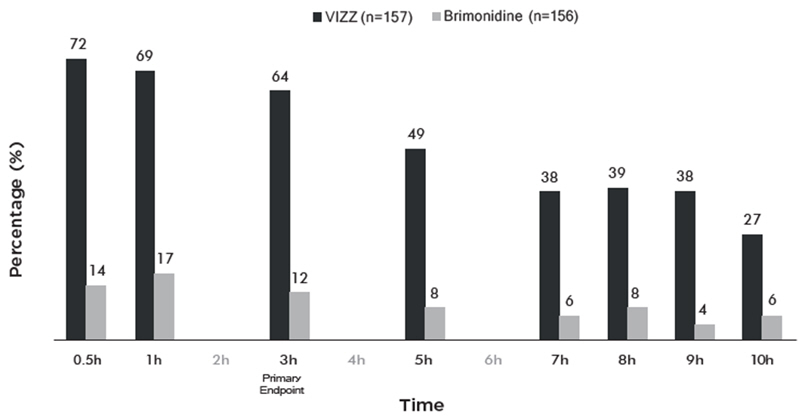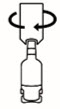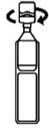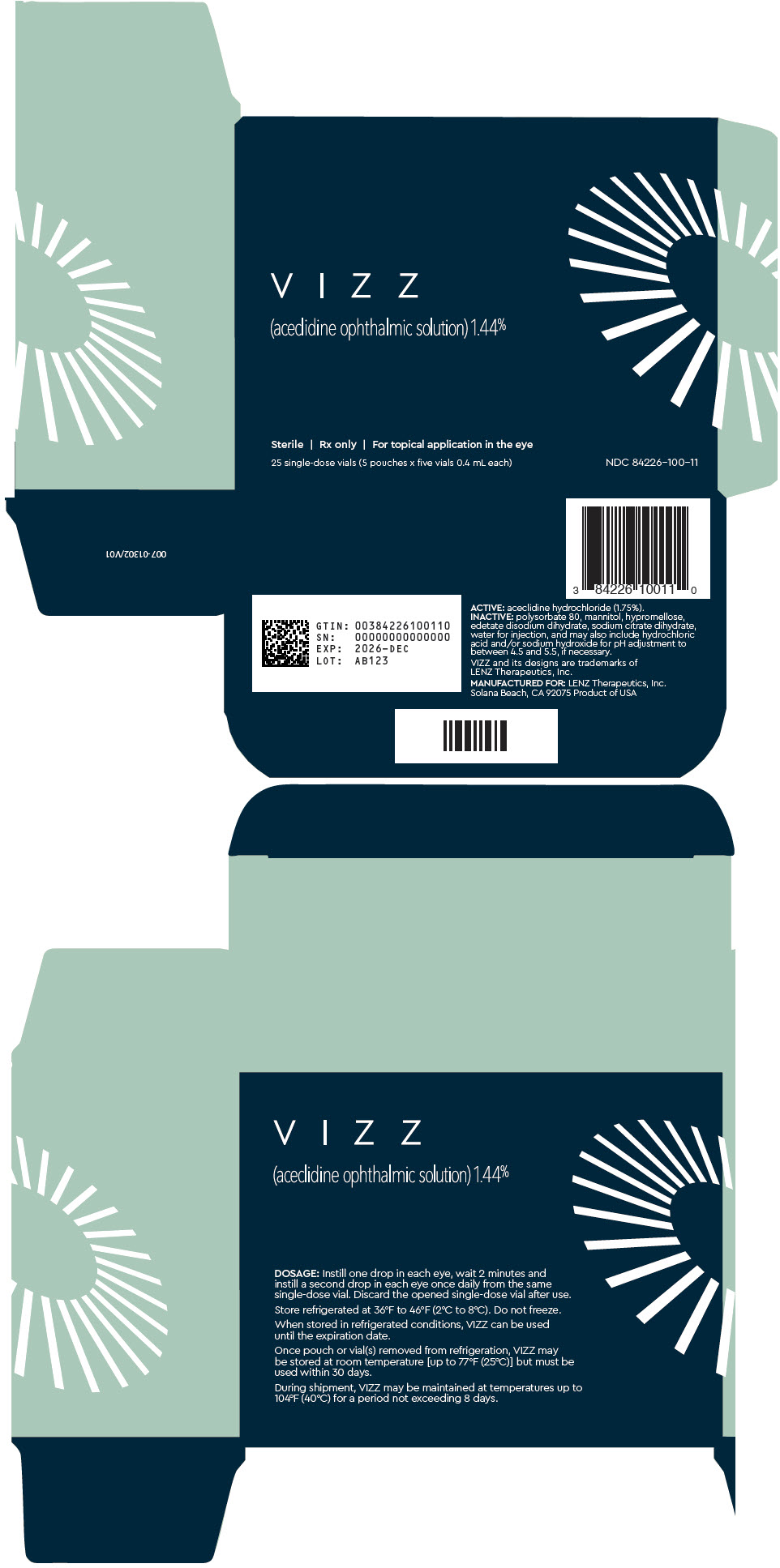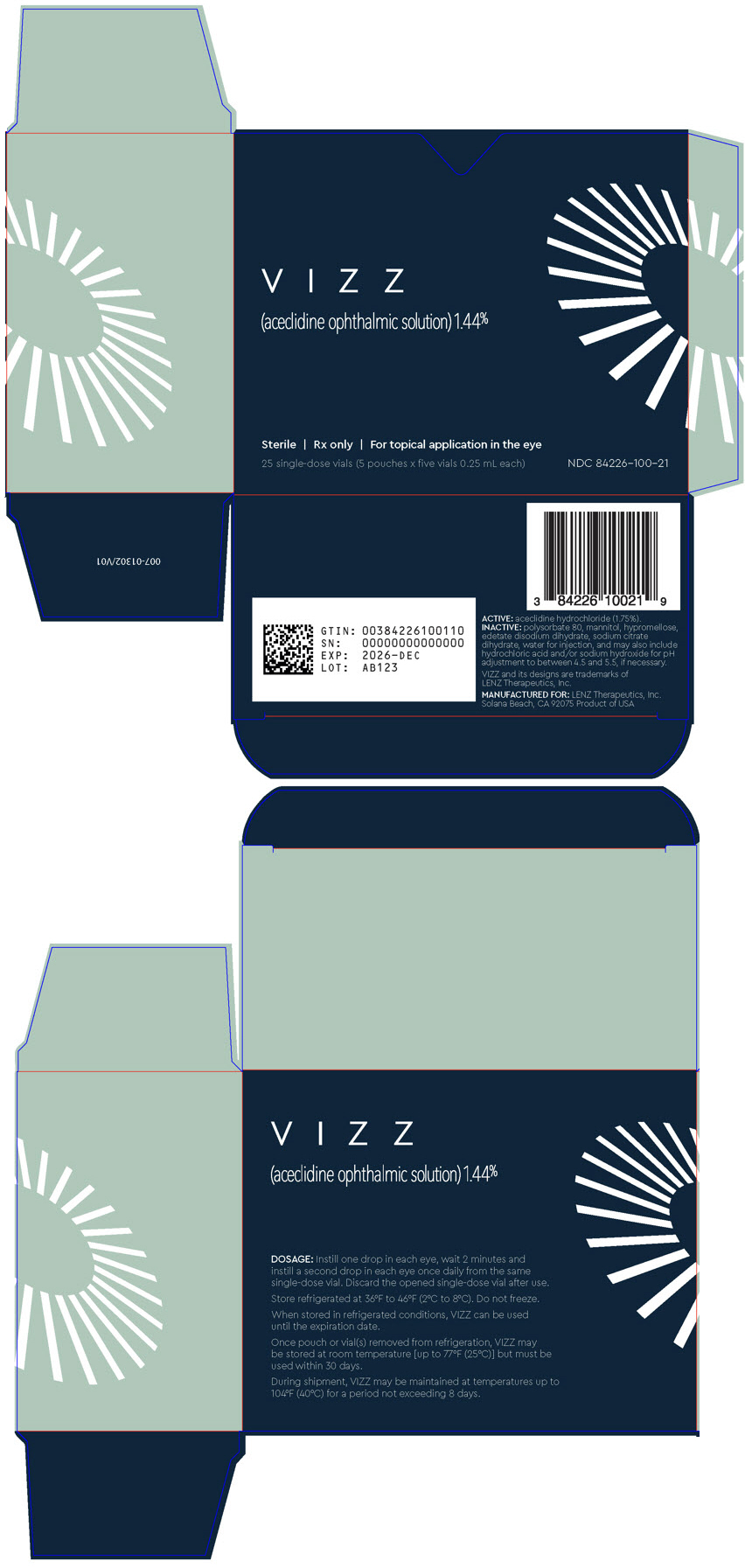 DRUG LABEL: VIZZ
NDC: 84226-100 | Form: SOLUTION/ DROPS
Manufacturer: LENZ Therapeutics, Inc.
Category: prescription | Type: HUMAN PRESCRIPTION DRUG LABEL
Date: 20260114

ACTIVE INGREDIENTS: ACECLIDINE HYDROCHLORIDE 14.66 mg/1 mL
INACTIVE INGREDIENTS: POLYSORBATE 80; MANNITOL; HYPROMELLOSE, UNSPECIFIED; EDETATE DISODIUM; TRISODIUM CITRATE DIHYDRATE; WATER; HYDROCHLORIC ACID; SODIUM HYDROXIDE

HIGHLIGHTS OF PRESCRIBING INFORMATION

These highlights do not include all the information needed to use VIZZ™ safely and effectively. See full prescribing information for VIZZ.
VIZZ (aceclidine ophthalmic solution) 1.44%, for topical ophthalmic use
Initial U.S. Approval: 2025

1 INDICATIONS AND USAGE

VIZZ is a cholinergic agonist indicated for the treatment of presbyopia in adults (1).

2 DOSAGE AND ADMINISTRATION

Instill one drop in each eye, wait 2 minutes and instill a second drop in each eye once daily (2).

3 DOSAGE FORMS AND STRENGTHS

Ophthalmic solution: aceclidine 1.44% in a single-dose vial (3).

4 CONTRAINDICATIONS

None.

5 WARNINGS AND PRECAUTIONS

- Blurred Vision:Patients may experience temporary dim or dark vision after instillation. Do not drive or operate machinery if vision is not clear (e.g., blurred vision). Exercise caution in night driving and other hazardous activities in poor illumination (5.1).
- Risk of Retinal Tear/Detachment:Rare cases of retinal tears and detachments have been reported with miotics. Examination of the retina is advised in all patients prior to initiation of therapy. Patients should be advised to seek immediate medical care with sudden onset of flashing lights, floaters, or vision loss (5.2).
- Iritis: Caution is advised in patients with a history of iritis (5.3).

6 ADVERSE REACTIONS

The most common adverse reactions were instillation site irritation (20%), dim vision (16%), and headache (13%) (6.1).

To report SUSPECTED ADVERSE REACTIONS, contact LENZ Therapeutics, Inc. at 1-888-711-LENZ or FDA at 1-800-FDA-1088 or www.fda.gov/medwatch.

FULL PRESCRIBING INFORMATION

1 INDICATIONS AND USAGE

VIZZ is indicated for the treatment of presbyopia in adults.

2 DOSAGE AND ADMINISTRATION

2.1 Recommended Dosage

Instill one drop in each eye, wait 2 minutes and instill a second drop in each eye once daily from the same single-dose vial.

2.2 Administration Instructions

Contact lenses should be removed prior to the instillation of VIZZ and may be reinserted 10 minutes after instillation.

If more than one topical ophthalmic product is being used, the products should be administered at least 5 minutes apart.

To open vial, twist off top [see How Supplied/Storage and Handling (16.1)] .

Discard the opened single-dose vial after use.

3 DOSAGE FORMS AND STRENGTHS

VIZZ is a clear to opalescent and colorless to slightly yellow ophthalmic solution containing 1.44% of aceclidine in a single-dose vial.

4 CONTRAINDICATIONS

None.

5 WARNINGS AND PRECAUTIONS

5.1 Blurred Vision

Miotics may cause accommodative spasm. Do not drive or operate machinery if vision is not clear (e.g., blurred vision).

Patients may experience temporary dim or dark vision. Exercise caution in night driving and other hazardous activities in poor illumination.

5.2 Risk of Retinal Tear/Detachment

Rare cases of retinal tear and detachment have been reported with miotics when used in susceptible individuals and those with pre-existing retinal disease. Examination of the retina is advised in all patients prior to the initiation of treatment with VIZZ. Patients should be advised to seek immediate care with sudden onset of flashing lights, floaters, or vision loss.

5.3 Iritis

Sequelae of ocular inflammation, i.e., adhesions (synechiae) between the iris and the lens, may be exacerbated with miotic use in patients with a known history of iritis.

5.4 Hypersensitivity

VIZZ is not recommended for use in patients with a known hypersensitivity to aceclidine or any other ingredient in VIZZ.

5.5 Use with Contact Lenses

Contact lenses should be removed prior to the instillation of VIZZ and may be reinserted 10 minutes after instillation.

5.6 Potential for Eye Injury or Contamination

To prevent eye injury or contamination, care should be taken to avoid touching the single-dose vial to the eye or to any other surface.

6 ADVERSE REACTIONS

6.1 Clinical Trials Experience

Because clinical trials are conducted under widely varying conditions, adverse reaction rates observed in the clinical trials of a drug cannot be directly compared to rates in the clinical trials of another drug and may not reflect the rates observed in practice.

VIZZ dosed once daily was evaluated for safety and efficacy in 466 participants with presbyopia in 2 randomized, double-masked, controlled phase 3 studies for 42 days (CLARITY-1, NCT05656027 and CLARITY-2, NCT05728944). VIZZ dosed once daily was also evaluated for long term safety in 217 participants with presbyopia in a separate randomized, double-masked, controlled phase 3 study (CLARITY-3, NCT05753189) for a 6-month duration.

The most common reported adverse reactions of participants were instillation site irritation (20%), dim vision (16%), and headache (13%). Adverse reactions reported in > 5% of participants were conjunctival hyperemia (8%) and ocular hyperemia (7%). The majority of adverse reactions were mild, transient, and self-resolving.

8 USE IN SPECIFIC POPULATIONS

8.1 Pregnancy

Risk Summary

There are no adequate and well controlled studies of VIZZ administration in pregnant women to inform a drug associated risk. In animal reproduction studies, oral administration of aceclidine to pregnant rats and rabbits throughout organogenesis and lactation did not produce adverse maternal, fetal or neonatal effects at clinically relevant doses.

Data

Animal Data

In embryofetal development studies, oral administration of aceclidine to pregnant rats and rabbits throughout organogenesis produced no maternal toxicity, skeletal anomalies, nor reduction in fetal body weight at 1.5 mg/kg/day (approximately 110-fold and 70-fold the human plasma exposure to the metabolite, 3-quinuclidinol, in rats and rabbits, respectively, at the MRHOD, assuming administration of 2 drops/eye/day).

In a pre-/postnatal development study in rats, oral administration of aceclidine during organogenesis through lactation produced no adverse maternal, fetal, or neonatal effects at doses up to 1.5 mg/kg/day (approximately 110-fold higher than the MHOD based on body surface area, assuming administration of 2 drops/eye/day).

8.2 Lactation

Risk Summary

There is no information regarding the presence of VIZZ or its metabolite in human or animal milk, the effects on breastfed infants or the effects on milk production to inform the risk of VIZZ to an infant during lactation.

Systemic levels of aceclidine and its metabolites following topical ocular administration are low [see Clinical Pharmacology (12.3)] , and it is not known whether measurable levels of aceclidine or its metabolites would be present in human milk following topical ocular administration.

The developmental and health benefits of breastfeeding should be considered along with the mother's clinical need for VIZZ and any potential adverse effects on the breastfed child from VIZZ or from the underlying maternal condition.

8.4 Pediatric Use

Presbyopia does not occur in the pediatric population.

8.5 Geriatric Use

No overall differences in safety or effectiveness of VIZZ have been observed between patients 65 years of age and older and younger adult patients.

10 OVERDOSAGE

Systemic toxicity following topical ocular administration of miotics is rare, but occasionally patients who are sensitive may develop increased salivation, sweating, gastrointestinal overactivity, and slowing of the pulse. Accidental ingestion can produce sweating, salivation, nausea, tremors, slowing of the pulse, and a decrease in blood pressure. In moderate overdosage, spontaneous recovery is to be expected and is aided by intravenous fluids to compensate for dehydration.

11 DESCRIPTION

VIZZ (aceclidine ophthalmic solution) 1.44% is a cholinergic muscarinic receptor agonist supplied as a sterile, clear to opalescent, colorless to slightly yellow, and viscous ophthalmic solution containing 1.75% of aceclidine hydrochloride (equivalent to 1.44% aceclidine).

The chemical names for aceclidine hydrochloride are: 1) 3-Acetoxyquinuclidine Hydrochloride; 2) 3-Quinuclidinyl Acetate Hydrochloride. Its molecular weight is 205.68 g/mol and its molecular formula is C9H15NO2∙ HCl.

Each mL of VIZZ contains aceclidine hydrochloride 1.75% (17.82 mg) as the active ingredient. Inactive ingredients in the ophthalmic solution are: polysorbate 80, mannitol, hypromellose, edetate disodium dihydrate, sodium citrate dihydrate, water for injection, and may also include hydrochloric acid and/or sodium hydroxide for pH adjustment to between 4.5 and 5.5, if necessary. VIZZ does not contain antimicrobial preservatives.

12 CLINICAL PHARMACOLOGY

12.1 Mechanism of Action

Aceclidine is a cholinergic muscarinic agonist that stimulates muscarinic receptors located on smooth muscles. VIZZ is a predominantly pupil selective miotic that interacts with the iris with minimal ciliary muscle stimulation. VIZZ causes contraction of the iris sphincter muscle, resulting in a pinhole effect that extends depth of focus to improve vision.

12.3 Pharmacokinetics

Aceclidine undergoes hydrolysis in the eye to acetate and 3-quinuclidinol (3-Q) with one mole of aceclidine hydrolyzed to one mole of 3-Q. Pharmacokinetic studies are performed on the analysis of 3-Q, which is a metabolite formed from the hydrolysis of aceclidine.

Systemic exposure of aceclidine hydrochloride was evaluated in 16 subjects with presbyopia following once daily VIZZ administration (one drop of VIZZ in each eye followed by a second drop in each eye two minutes later) for 8 days. The mean Cmaxand AUC0-tvalues for 3-Q after Day 8 dosing were 2.114 ng/mL and 4.899 hr*ng/mL, respectively.

There was little to no accumulation of 3-Q after repeat once daily dosing of VIZZ. After 8 days, the mean (SD) RAUC0-tand RCmaxvalues were 1.189 (0.770) and 0.996 (0.314), respectively. T1/2could not be estimated at any timepoint due to the limited amount of quantifiable 3-Q concentrations after ocular dosing.

13 NONCLINICAL TOXICOLOGY

13.1 Carcinogenesis, Mutagenesis, Impairment of Fertility

Carcinogenesis

Long term studies in animals have not been performed to evaluate carcinogenic potential.

Mutagenesis

Aceclidine did not show any potential to cause genetic toxicity in a series of studies that included: 1) bacterial assays (Salmonella and E. coli) for reverse gene mutations; 2) an in vitro chromosome aberration assay in cultured human peripheral blood lymphocytes; and 3) an in vivo chromosome aberration assay (micronucleus test) in mice.

Impairment of Fertility

Oral administration of aceclidine produced no adverse effect on fertility in rats at doses up to 1.5 mg/kg/day (approximately 25 times the MRHOD based on body surface area).

14 CLINICAL STUDIES

The efficacy of VIZZ for the treatment of presbyopia was demonstrated in two, randomized, double-masked, controlled studies, CLARITY-1 and CLARITY-2. A total of 466 participants aged 45 to 75 years old with presbyopia were randomized. Participants had a refractive range from -4.00 to +1.00 D sphere, with astigmatism up to 2.00 D, and a spherical equivalent no more myopic than -4.00 D. Both studies included participants who were post-refractive surgery and/or pseudophakic.

Participants were instructed to instill 2 drops of VIZZ (or control) in each eye once daily, one drop in each eye followed by a second drop in each eye two minutes later. Participants were treated for 42 days. Ophthalmic efficacy assessments were conducted on Day 1, Day 15, and Day 28 of the study at various timepoints through 10 hours post dose.

In each study, the proportion of participants gaining 3 lines or more in high contrast, distance corrected, near visual acuity (DCNVA) at 40 cm, without loss of 1 line or more (≥5 letters) of distance corrected, distance visual acuity (DCDVA) at 4 meters was statistically significantly greater in the VIZZ group compared to the control group at Day 1, Hour 3.

Table 1. Primary Efficacy Endpoint from CLARITY-1 and CLARITY-2 Studies Day 1, at 3 Hours Post Dose (FAS Population)
 | CLARITY-1 |  |  | CLARITY-2
 | VIZZ N=157 | Brimonidine N=156 | p-value | VIZZ N=77 | Vehicle N=76 | p-value
Proportion of participants gaining 3-lines or more in DCNVA at 40cm, without losing 1 line or more (≥5 letters) of DCDVA at 4m at Day 1, at 3 hours | 65% | 12% | p<0.01 | 71% | 8% | p<0.01

Figure 1 and Figure 2 demonstrate the onset of the VIZZ effect on presbyopia, from 30 minutes post dose and lasting 10 hours.

Figure 1 Percentage of Participants Achieving 3 Lines or More Improvement in High Contrast, Monocular Near Vision (DCNVA at 40 cm) and No Loss of 1 or More Lines (DCDVA at 4 m) on Day 1 at All Measured Time Points (CLARITY-2, FAS population with Observed data)

Figure 2 Percentage of Participants Achieving 3 Lines or More Improvement in High Contrast, Monocular Near Vision (DCNVA at 40 cm) and No Loss of 1 or More Lines (DCDVA at 4 m) on Day 1 at All Measured Time Points (CLARITY-1, FAS population with Observed data)

16 HOW SUPPLIED/STORAGE AND HANDLING

16.1 How Supplied

VIZZ (aceclidine ophthalmic solution) 1.44% is supplied as a sterile, clear to opalescent, colorless to slightly yellow, and viscous ophthalmic solution in configurations of 5 single-dose vials. VIZZ does not include antimicrobial preservatives.

Each single-dose vial is comprised of transparent low-density polyethylene (LDPE).

5 single-dose vials are packaged in a foil pouch.

VIZZ is supplied in:

NDC Number | Description | Vial Configuration
84226-100-11 | carton box of 25 single-dose vials (5 pouches x five vials of 0.4 mL each)
84226-100-21 | carton box of 25 single-dose vials (5 pouches x five vials of 0.25 mL each)

16.2 Storage and Handling

Store refrigerated at 36°F to 46°F (2°C to 8°C). Do not freeze.

When stored in refrigerated conditions, VIZZ can be used until the expiration date.

Once pouch or vial(s) are removed from refrigeration, VIZZ may be stored at room temperature [up to 77°F (25°C)] but must be used within 30 days.

Discard the opened single-dose vial after use.

During shipment, VIZZ may be maintained at temperatures up to 104°F (40°C) for a period not exceeding 8 days.

17 PATIENT COUNSELING INFORMATION

Night Driving

Advise patients that they may experience temporary dim or dark vision. Advise patients to exercise caution with night driving and when hazardous activities are undertaken in poor illumination [see Warnings and Precautions (5.1)].

Blurred Vision

Temporary problems when changing focus between near and distant objects may occur. Advise patients not to drive or use machinery if vision is not clear (e.g., blurred vision) [see Warnings and Precautions (5.1)] .

When to Seek Physician Advice

Advise patients to seek immediate medical care with sudden onset of flashing lights, floaters, or vision loss [see Warnings and Precautions (5.2)].

Contact Lens Wear

Advise patients to remove contact lenses prior to the instillation of VIZZ. Wait 10 minutes after instillation before reinserting their contact lenses [see Warnings and Precautions (5.5)].

Potential for Eye Injury or Contamination

Advise patients to avoid touching the tip of the single-dose vial to the eye or to any other surface in order to prevent eye injury or contamination [see Warnings and Precautions (5.6)]. Advise patients to discard the opened single-dose vial and any remaining contents after use.

Concomitant Topical Ocular Therapy

Advise patients if more than one topical ophthalmic medication is being used, the medicines should be administered at least 5 minutes apart [see Dosage and Administration (2)] .

U.S. Patent Nos.: 11,179,328, 10,052,313, 9,844,537, 12,128,036, and 12,414,942.

VIZZ is a registered trademark of LENZ Therapeutics, Inc.
Manufactured for: LENZ Therapeutics, Inc., 201 Lomas Santa Fe Drive, Suite 300, Solana Beach, CA 92075, USA

PRINCIPAL DISPLAY PANEL - 0.4 mL Vial Pouch Carton

VIZZ
(aceclidine ophthalmic solution) 1.44%

Sterile | Rx only | For topical application in the eye
25 single-dose vials (5 pouches x ﬁve vials 0.4 mL each)

NDC 84226-100-11

PRINCIPAL DISPLAY PANEL - 0.25 mL Vial Pouch Carton

VIZZ
(aceclidine ophthalmic solution) 1.44%

Sterile | Rx only | For topical application in the eye
25 single-dose vials (5 pouches x ﬁve vials 0.25 mL each)

NDC 84226-100-21